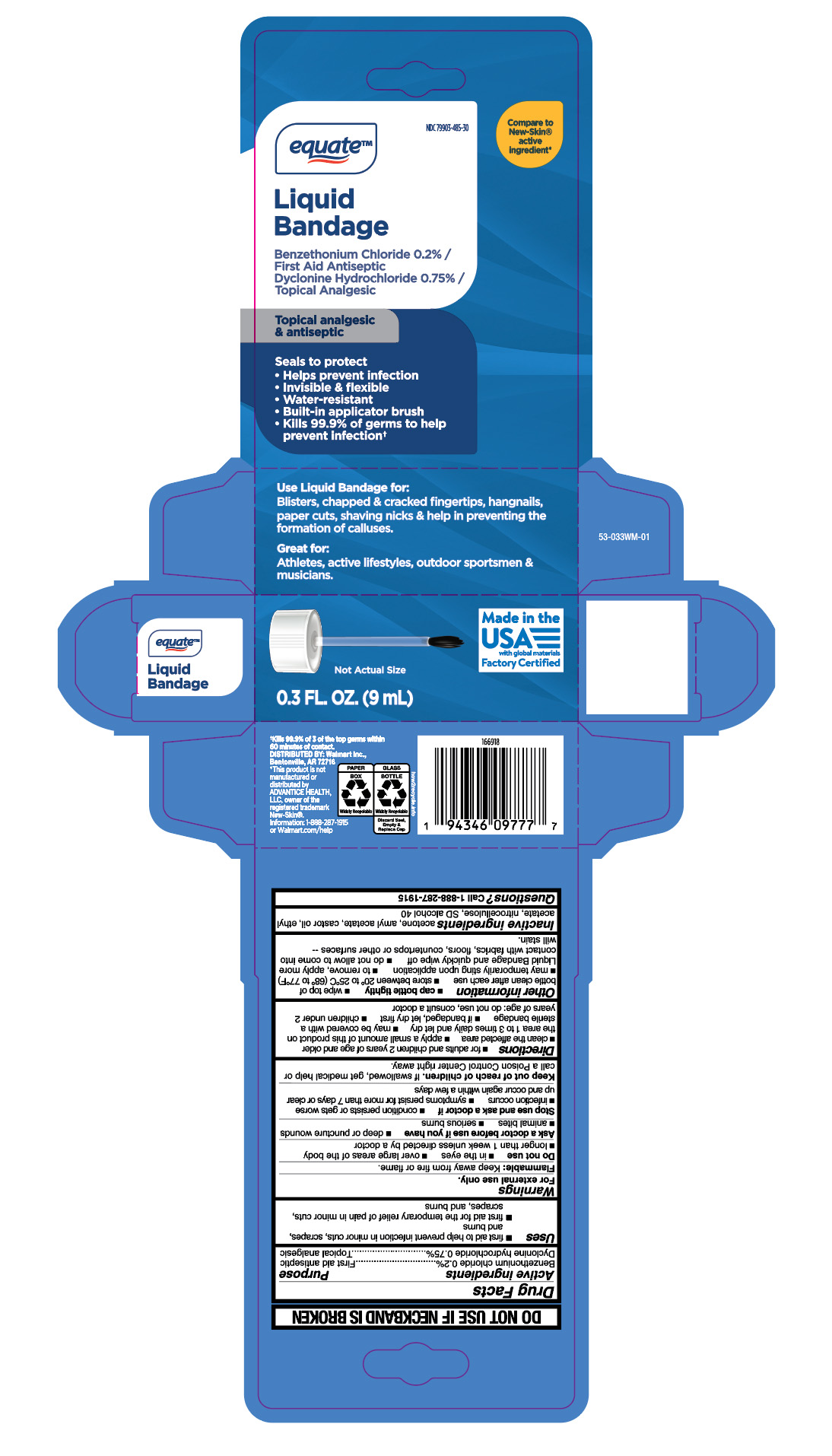 DRUG LABEL: Liquid Bandage
NDC: 79903-485 | Form: LIQUID
Manufacturer: Wal-Mart Stores, Inc.
Category: otc | Type: HUMAN OTC DRUG LABEL
Date: 20260129

ACTIVE INGREDIENTS: BENZETHONIUM CHLORIDE 0.06 mg/29.6 mL; DYCLONINE HYDROCHLORIDE 0.23 mg/29.6 mL
INACTIVE INGREDIENTS: ACETONE; AMYL ACETATE; CASTOR OIL; ETHYL ACETATE; PYROXYLIN; ALCOHOL

Equate Liquid Bandage

Active ingredients

Benzethonium chloride 0.2%
Dyclonine hydrochloride 0.75%

Purpose

First aid antiseptic
Topical analgesic

Uses

- first aid to help prevent infection in minor cuts, scrapes, and bums
- first aid for the temporary relief of pain in minor cuts, scrapes, and burns

Warnings

For external use only.

Flammable:

Keep away from fire or flame.

Do not use

- in the eyes
- over large areas of the body
- longer than 1 week unless directed by a doctor

Ask a doctor before use if you have

- deep or puncture wounds
- animal bites
- serious burns

Stop use and ask a doctor if

- conditions persists or gets worse
- infection occurs
- symptoms persists for more than 7 days or clear up and occur again within a few days

Keep out of reach of children.

If swallowed, get medical help or call a Poison Control Center right away.

Directions

- for adults and children 2 years of age and older
- clean the affected area
- apply a small amount of this product on the area 1 to 3 times daily and let dry
- may be covered with a sterile bandage
- if bandaged, let dry first
- children under 2 years of age: do not use, consult a doctor

Other information

- cap bottle tightly
- wipe top of bottle clean after each use
- store between 20° to 25°C (68° to 77°F)
- may temporarily sting upon application
- to remove, apply more Liquid Bandages and quickly wipe off
- do not allow to come into contact with fabrics, floors, countertops or other surfaces -- will stain.

Inactive ingredients

acetone, amyl acetate, castor oil, ethyl acetate, nitrocellulose, SD slcohol 40

Questions

Call 1-888-287-1915

RECENT MAJOR CHANGES

.

Principal Display Panel

equate

Liquid

Bandage

Benzethonium chloride 0.2% /

First Aid Antiseptic
Dyclonine hydrochloride 0.75% /

Topical Analgesic

Topical analgesic

& antiseptic

Seals to protect

- Helps prevent infection
- Invisible & flexible
- Water- resistant
- Built-in applicator brush
- Kills 99.9% of germs to help
  prevent infectiont

0.3 FL. OZ. (9 mL)